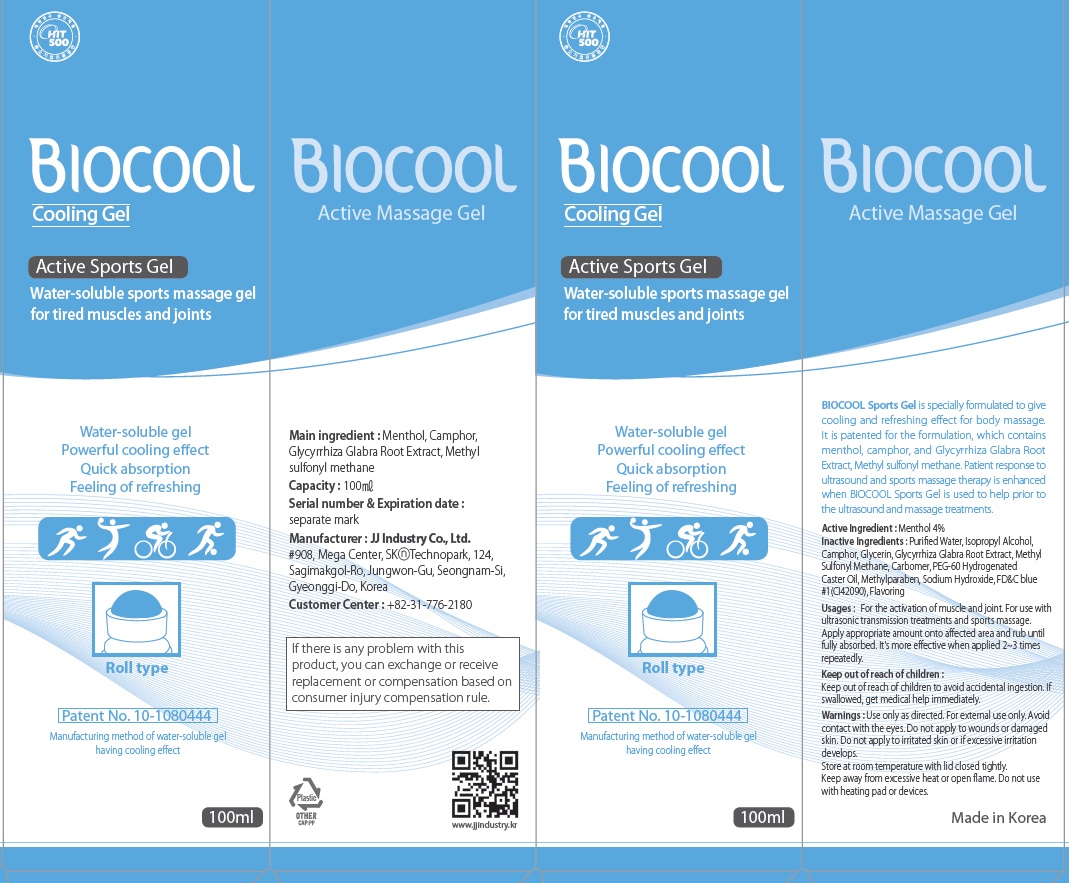 DRUG LABEL: BIOCOOL
NDC: 70612-020 | Form: GEL
Manufacturer: JJindustry.Co.Ltd
Category: otc | Type: HUMAN OTC DRUG LABEL
Date: 20160419

ACTIVE INGREDIENTS: Menthol 4.0 g/100 mL
INACTIVE INGREDIENTS: Water; Glycerin

ACTIVE INGREDIENT

Active Ingredient: Menthol 4%

INACTIVE INGREDIENT

Inactive Ingredients: Purified Water, Isopropyl Alcohol, Camphor, Glycerin, Glycyrrhiza Glabra Root Extract, Methyl sulfonyl methane, Carbomer, PEG-60 Hydrogenated Caster Oil, Methylparaben, Sodium Hydroxide, FD&C blue #1(CI42090), Flavoring.

PURPOSE

Purpose: BIOCOOL Sports Gel is specially formulated for the temporary activation from muscle and joint stiffness through cooling and refreshing effect. It is patented for the formulation, which contains Menthol, Camphor, and Glycyrrhiza Glabra Root Extract, Methyl sulfonyl methane. Patient response to ultrasound and sports massage therapy is enhanced when BIOCOOL Sports Gel is used to help prior to the ultrasound and massage treatments.

WARNINGS

Warnings: Use only as directed. For external use only. Avoid contact with the eyes. Do not apply to wounds or damaged skin. Do not apply to irritated skin or if excessive irritation develops. Store at room temperature with lid closed tightly. Keep away from excessive heat or open flame. Do not use with heating pads or devices.

Keep out of reach of children: Keep out of reach of children to avoid accidental ingestion. If swallowed, get medical help immediately.

Usages

Usages: For the activation of muscle and joint. For use with ultrasonic transmission treatments and sports massage. Apply appropriate amount onto affected area and rub until fully absorbed. It's more effective when applied 2~3 times repeatedly.

Usages

Usages: For the activation of muscle and joint. For use with ultrasonic transmission treatments and sports massage. Apply appropriate amount onto affected area and rub until fully absorbed. It's more effective when applied 2~3 times repeatedly.